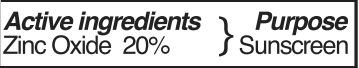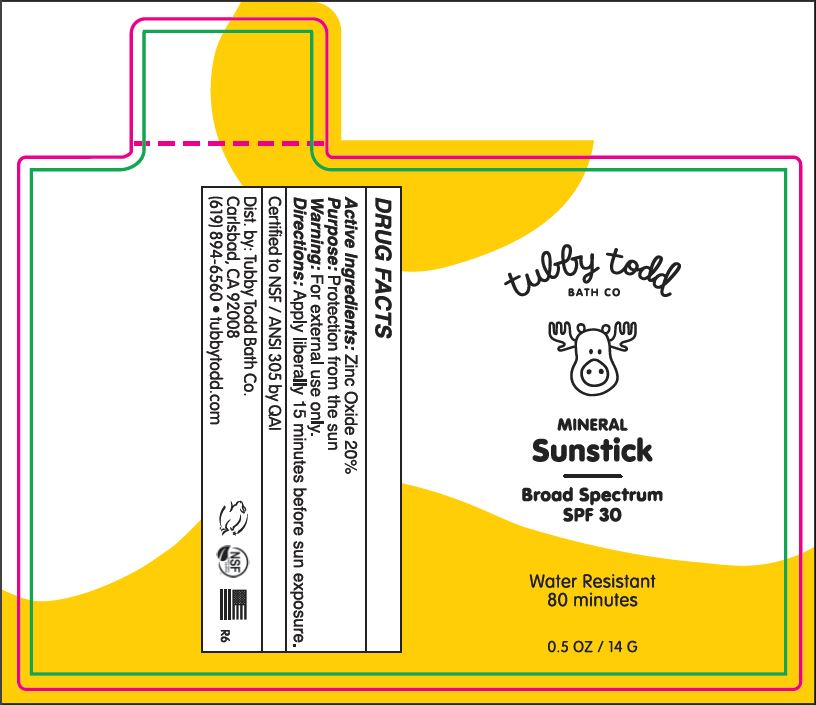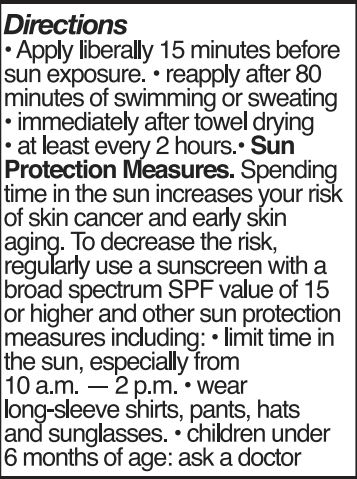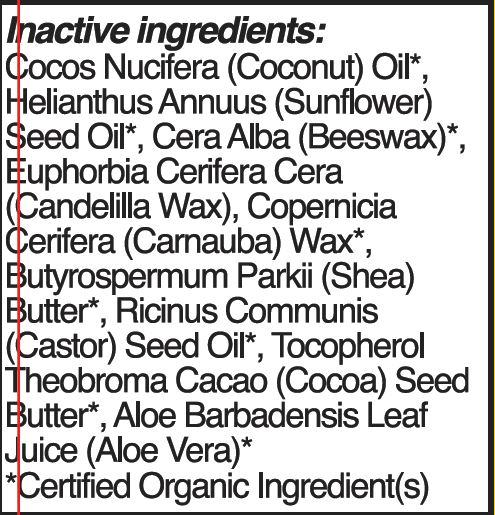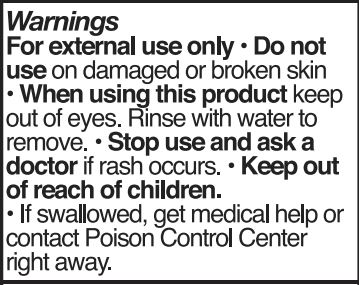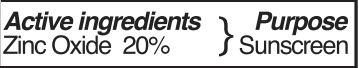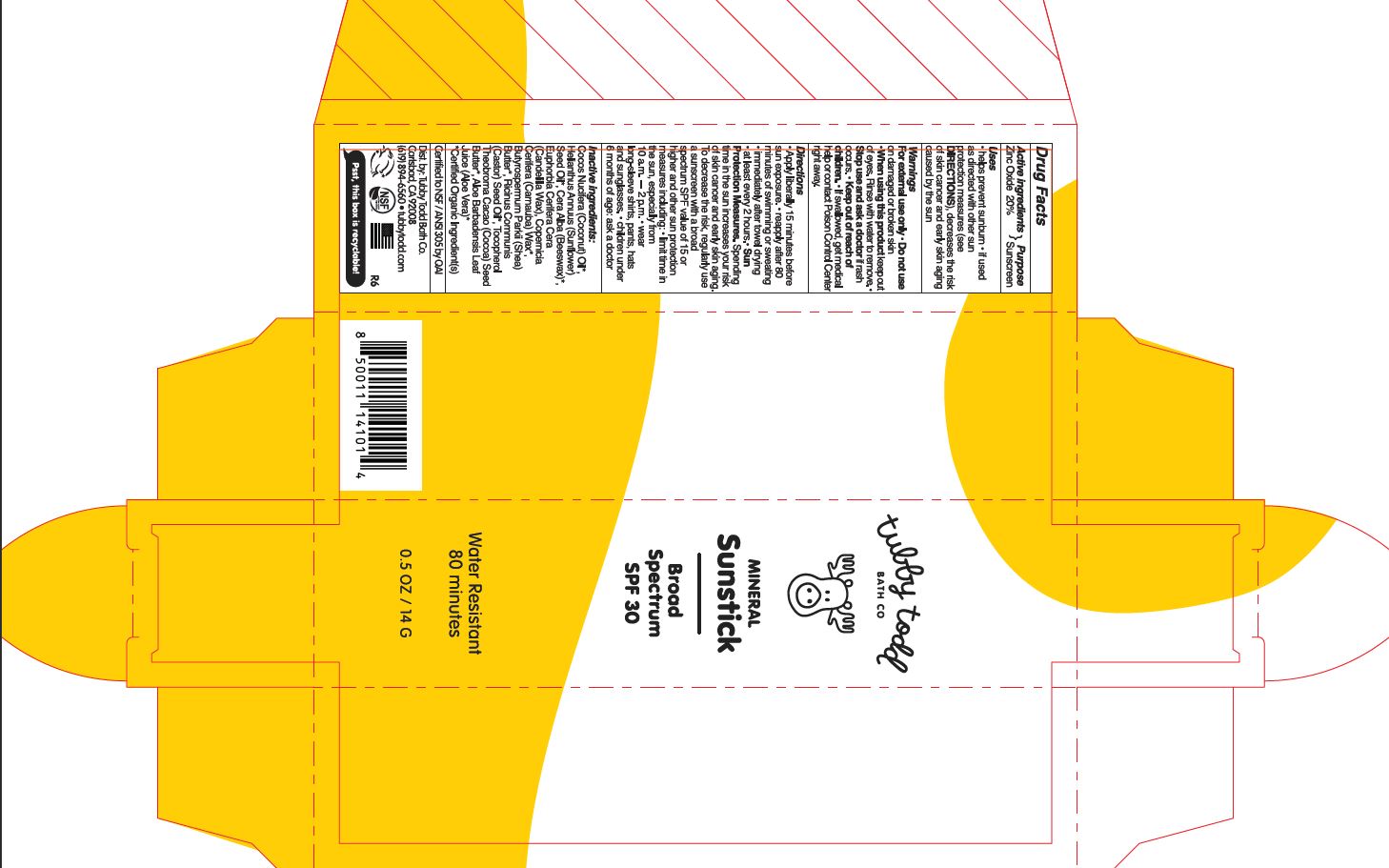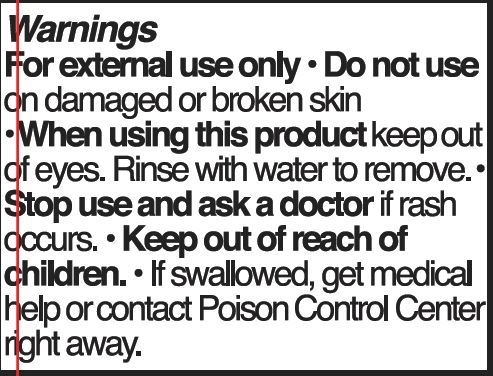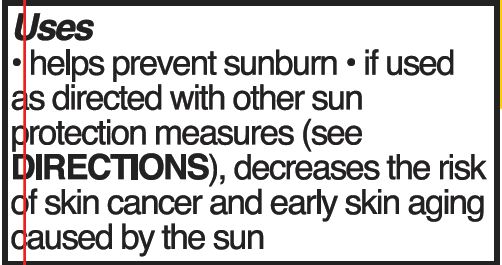 DRUG LABEL: SUNSCREEN
NDC: 62932-202 | Form: STICK
Manufacturer: Private Label Select Ltd CO
Category: otc | Type: HUMAN OTC DRUG LABEL
Date: 20220104

ACTIVE INGREDIENTS: ZINC OXIDE 20 g/100 g
INACTIVE INGREDIENTS: .ALPHA.-TOCOPHEROL, D-; .GAMMA.-TOCOPHEROL; .DELTA.-TOCOPHEROL; ALOE VERA LEAF; .BETA.-TOCOPHEROL; CANDELILLA WAX; CARNAUBA WAX; CASTOR OIL; COCOA BUTTER; COCONUT OIL; WHITE WAX; SUNFLOWER OIL; SHEA BUTTER

Tubby Todd Play Mineral Sunstick, SPF 30